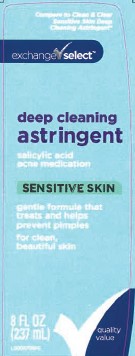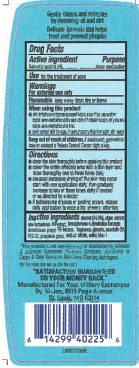 DRUG LABEL: Salicylic Acid
NDC: 55301-875 | Form: LIQUID
Manufacturer: Your Military Exchanges
Category: otc | Type: HUMAN OTC DRUG LABEL
Date: 20260212

ACTIVE INGREDIENTS: SALICYLIC ACID 5 mg/1 mL
INACTIVE INGREDIENTS: ALCOHOL; LAMINARIA DIGITATA; ALOE VERA LEAF; SULISOBENZONE; DENATONIUM BENZOATE; POLYETHYLENE GLYCOL 1500; GLYCERIN; ISOCETETH-20; PROPYLENE GLYCOL; SODIUM CITRATE; WATER; FD&C BLUE NO. 1

Exchange Select 875.002/875AE
Astringent

Claims

Gently cleans and refreshes by removing oil and dirt.

Delicate formula that helps treat and prevent pimples.

Active ingredient

Salicylic acid 0.5%

Purpose

Acne medication

Use

for the treatment of acne

Warnings

For external use only

Flammable. Keep away from fire or flame.

When using this product

- skin irritation and dryness is more likely to occur if you use another topical acne medication at the same time. If irritation occurs, only use one topical acne medication at a time
- avoid contact with the eyes. If contact occurs, flush thoroughly with water.

Keep out of reach of children.

If swallowed, get medical help or contact a Poison Control Center right away.

Directions

- clean the skin thoroughly before applying this product
- cover the entire affected area with a thin layer and rinse thoroughly one to three times daily
- because excessive drying of the skin may occur, start with one application daily, then gradually increase to two or three times daily if needed or as directed by a doctor
- if bothersome dryness or peeling occurs, reduce daily application to once a day or every other day

Inactive ingredients

alcohol (24.5%), algae extract, aloe barbadesis leaft extract, benzophenone-4, denatonium benzoate, dimethicone propyl PG-betaine, fragrance, glycerin, isoceteth-20, PEG-32, propylene glycol, sodium citrate, water, blue 1

Disclaimer

*This product is not manufactured or distributed by Johnson & Johnson Consumer Products Company, distributor of Clean & Clear Sensitive Skin Deep Cleaning Astringent.

ADVERSE REACTION

"SATISFACTION GUARANTEED OR YOUR MONEY BACK."

Manufactured For Your Military Exchanges

By: Vi-Jon, 8515 Page Avenue

St. Louis, MO 63114

DSP-TN-15000 DSP-MO-34 SDS-TN-15012

Principal Display Panel

Compare to Clean & Clear Sensitive Skin Deep Cleaning Astringent*

exchange select™

deep cleaning astringent

salicylic acid

acne medication

SENSITIVE SKIN

gentle formula that treats and helps prevent pimples

for clean, beautiful skin

8 FL OZ (237 mL)

quality value